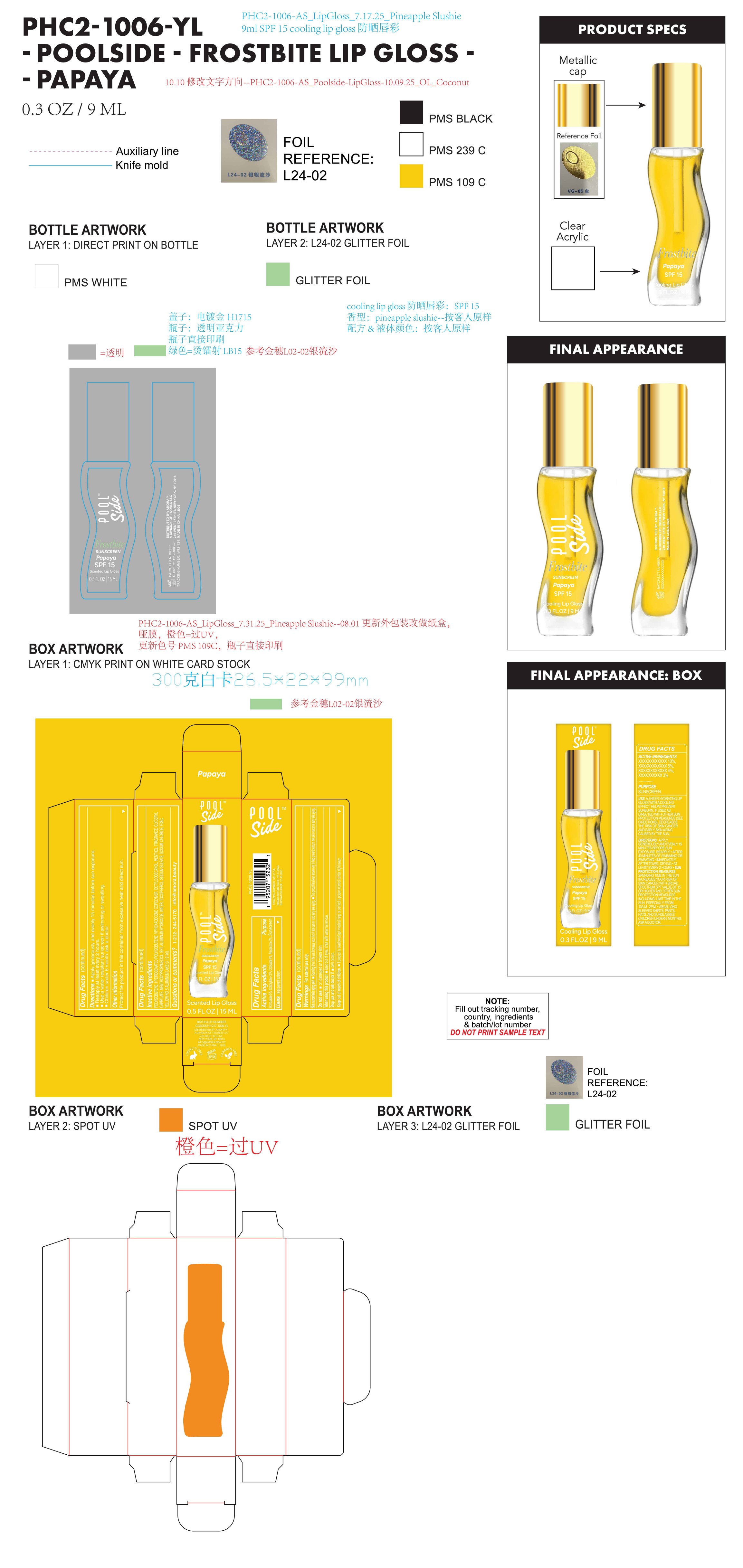 DRUG LABEL: Poolside Frostbite Sunscreen Papaya SPF 15 Scented lip gloss
NDC: 85161-159 | Form: LIQUID
Manufacturer: Longway Technology(Guangzhou)Co.,Ltd.
Category: otc | Type: HUMAN OTC DRUG LABEL
Date: 20251204

ACTIVE INGREDIENTS: HOMOSALATE 0.05 g/1 mL; OCTOCRYLENE 0.045 g/1 mL; AVOBENZONE 0.03 g/1 mL; OCTISALATE 0.04 g/1 mL
INACTIVE INGREDIENTS: MENTHOXYPROPANEDIOL; SODIUM SULFATE; SODIUM CHLORIDE; POLYISOBUTYLENE (1300 MW); HYDROGENATED POLYISOBUTENE (450 MW); VP/HEXADECENE COPOLYMER; OCTYLDODECANOL; TOCOPHEROL; BHT; GLYCERYL CAPRYLATE; ALUMINUM HYDROXIDE; MENTHOL; FRAGRANCE 13576; WATER; CI 19140

ACTIVE INGREDIENT

Homosalate 5%, Octocrylene 4.5%, Octisalate 4%, Avobenzone 3%

PURPOSE

Sunscreen

INDICATIONS AND USAGE

Helps prevent sunburn

WARNINGS

For external use only.
Skin cancer/skin aging alert.

Spending time in the sun increases your risk of skin cancer and early skin aging.

This product has been shown only to help prevent sunburn, not skin cancer or early skin aging.

Do not use on damaged or broken skin.

When using this product keep out of eyes. rinse with water to remove.

Stop use and ask doctor if rash occurs.

Keep out of reach of children. If product is swallowed get medical help or contact a poison control center right away

QUESTIONS

1-212-244-5170 info@amora.beauty

INACTIVE INGREDIENT

POLYISOBUTENE, HYDROGENATED POLYISOBUTENE, VP/HEXADECENE COPOLYMER, OCTYLDODECANOL, MENTHOL, FRAGRANCE, GLYCERYL CAPRYLATE, MENTHOXYPROPANEDIOL, BHT, ALUMINUM HYDROXIDE, WATER, TOCOPHEROL, SODIUM SULFATE, SODIUM CHLORIDE, FD&C YELLOW NO. 5 ALUMINUM LAKE(CI 19140).

OTHER SAFETY INFORMATION

Protect the product in this container from excessive heat and direct sun.

DOSAGE AND ADMINISTRATION

Apply generously and evenly 15 minutes before sun exposure.

Reapply at least every 2 hours.

Use a water resistant sunscreen if swimming or sweating.

Children under 6 month: ask a doctor.

KEEP OUT OF REACH OF CHILDREN

If product is swallowed get medical help or contact a poison control center right away